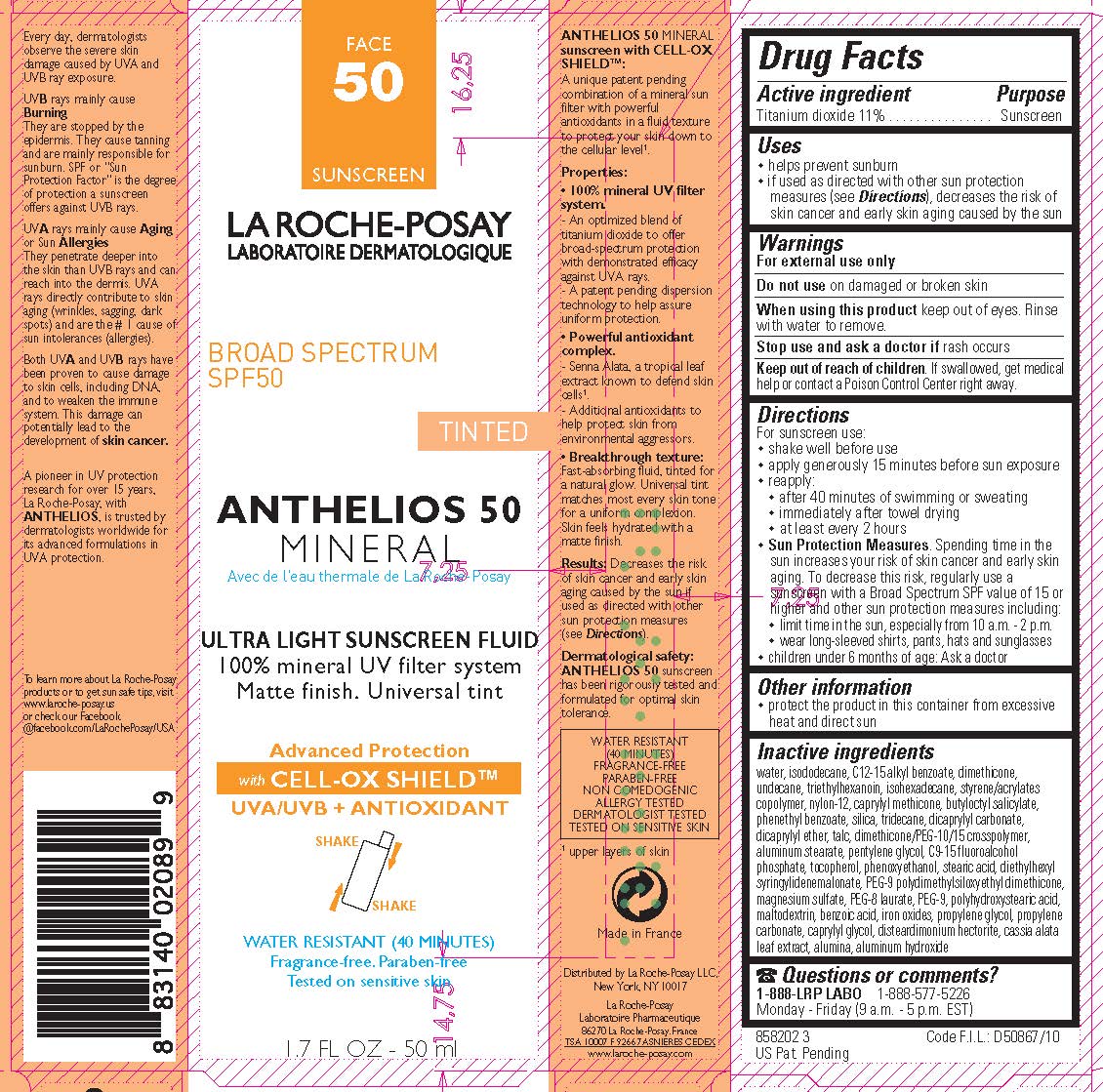 DRUG LABEL: La Roche Posay Laboratoire Dermatologique Anthelios 50 Tinted Mineral Sunscreen Broad Spectrum SPF 50
NDC: 69625-899 | Form: LOTION
Manufacturer: Cosmetique Active Production
Category: otc | Type: HUMAN OTC DRUG LABEL
Date: 20240115

ACTIVE INGREDIENTS: TITANIUM DIOXIDE 110 mg/1 mL
INACTIVE INGREDIENTS: WATER

Drug Facts

Active ingredient

Titanium dioxide 11%

Purpose

Sunscreen

Uses

- helps prevent sunburn
- if used as directed with other sun protection measures (see Directions), decreases the risk of skin cancer and early skin aging caused by the sun

Warnings

For external use only

Do not use

on damaged or broken skin

When using this product

keep out of eyes. Rinse with water to remove.

Stop use and ask a doctor if

rash occurs

Keep out of reach of children.

If swallowed, get medical help or contact a Poison Control Center right away.

Directions

For sunscreen use:

- shake well before use

- apply generously 15 minutes before sun exposure

- reapply:

- after 40 minutes of swimming or sweating
- immediately after towel drying
- at least every 2 hours

Sun Protection Measures. Spending time in the sun increases your risk of skin cancer and early skin aging. To decrease this risk, regularly use a sunscreen with a Broad Spectrum SPF value of 15 or higher and other sun protection meausures including:

- limit time in the sun, especially from 10 a.m. - 2 p.m.

- wear long-sleeved shirts, pants, hats and sunglasses

- children under 6 months of age: Ask a doctor

Other information

protect the product in this container from excessive heat and direct sun

Inactive ingredients

water, isododecane, C12-15 alkyl benzoate, dimethicone, undecane, triethylhexanoin, isohexadecane, styrene/acrylates copolymer, nylon-12, caprylyl methicone, butyloctyl salicylate, phenethyl benzoate, silica, tridecane, dicaprylyl carbonate, dicaprylyl ether, talc, dimethicone/PEG-10/15 crosspolymer, aluminum stearate, pentylene glycol, C9-15 fluoroalcohol phosphate, tocopherol, phenoxyethanol, stearic acid, diethylhexyl syringylidenemalonate, PEG-9 polydimethylsiloxyethyl dimethcone, magnesium sulfate, PEG-8 laurate, PEG-9, polyhydroxystearic acid, maltodextrin, benzoic acid, iron oxides, propylene glycol, propylene carbonate, caprylyl glycol, disteardimonim hectorite, cassia alata leaf extract, alumina, aluminum hydroxide

Questions or comments?

1-888-577-5226 1-888-LRP LABO

Monday - Friday (9 a.m. - 5 p.m. EST)